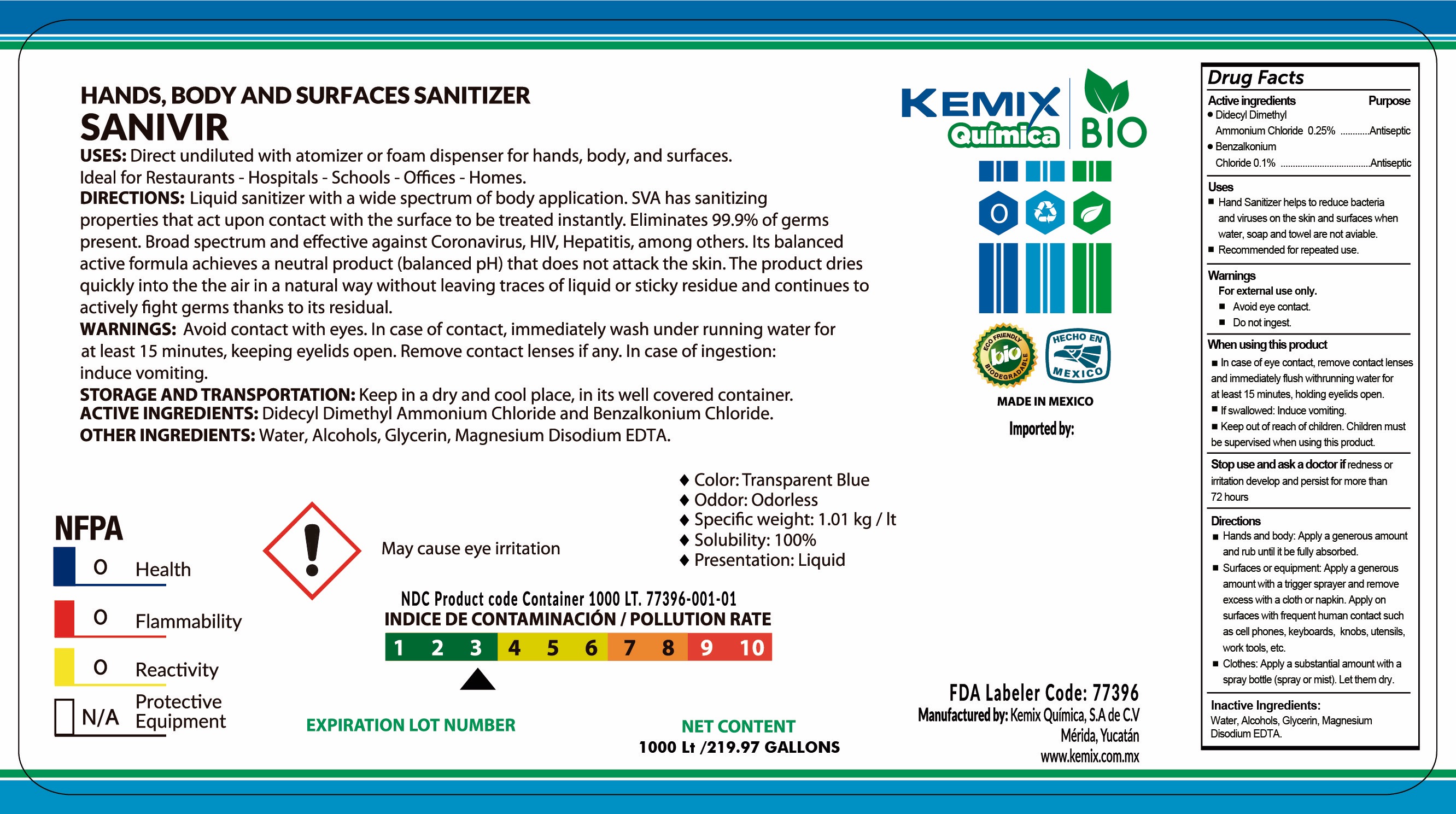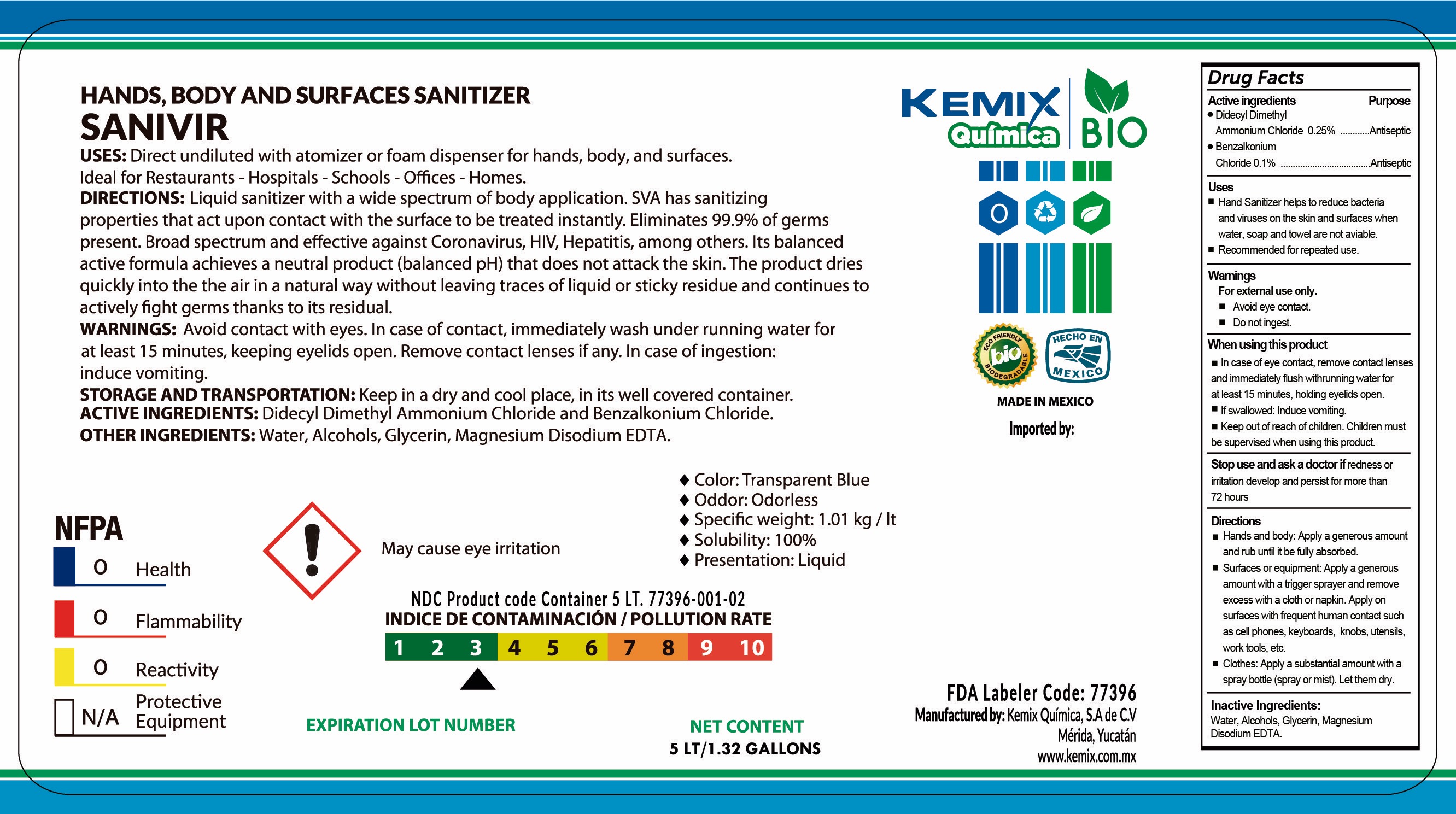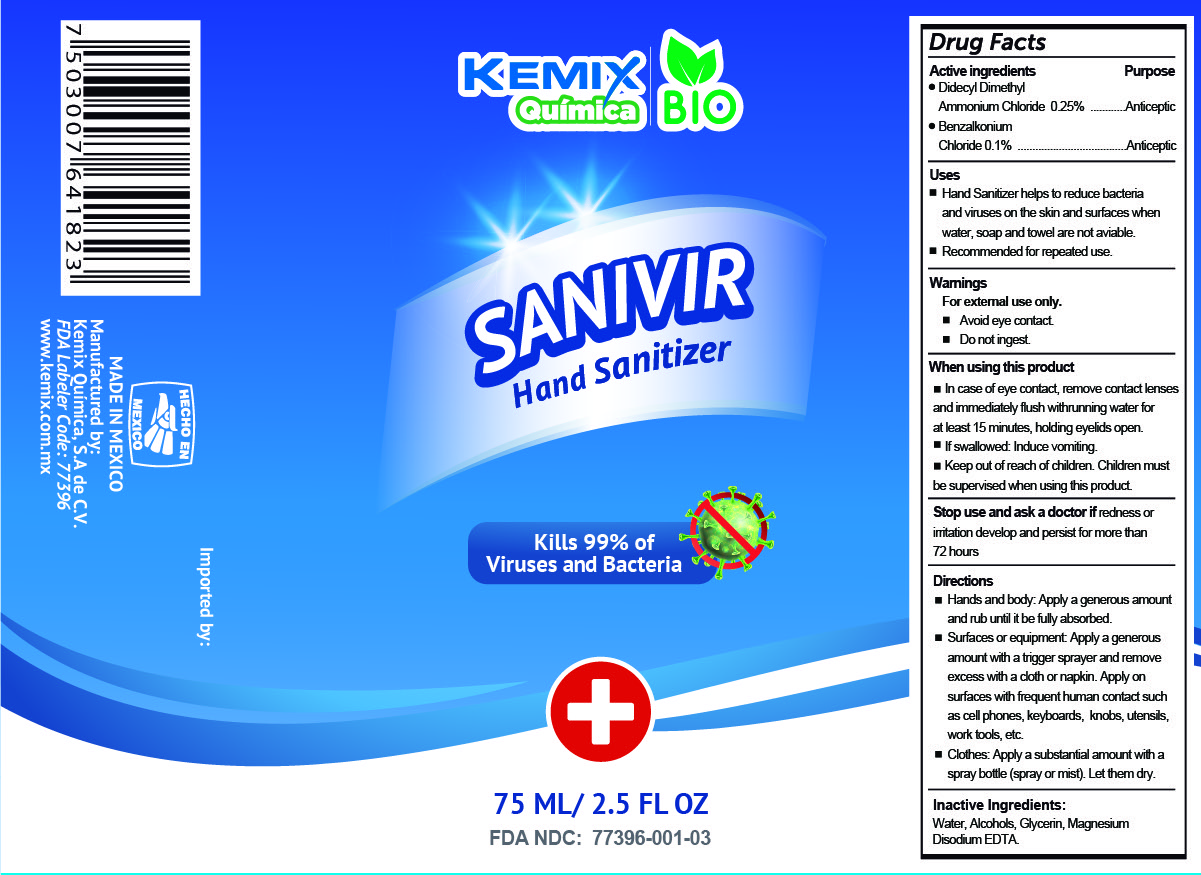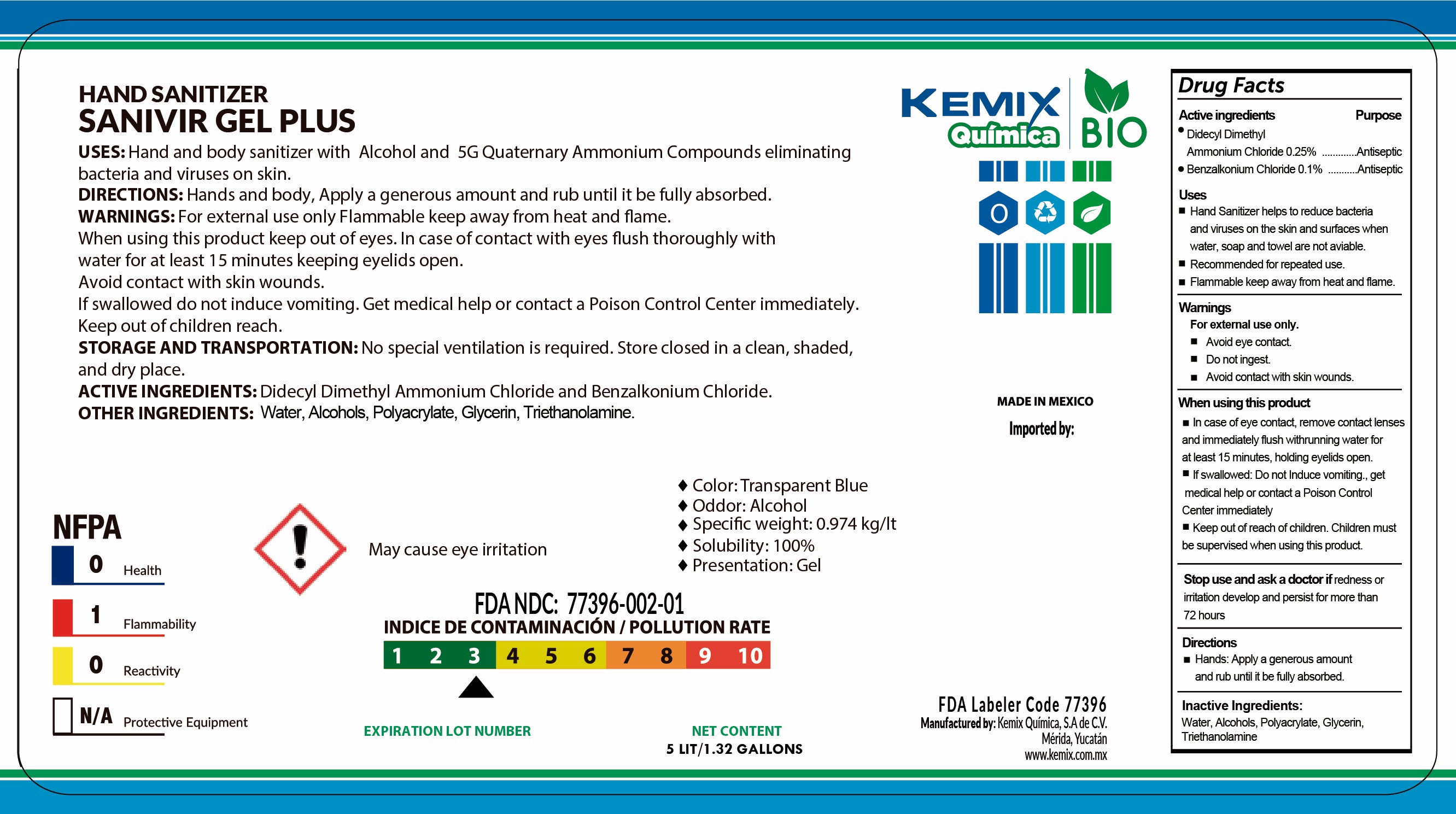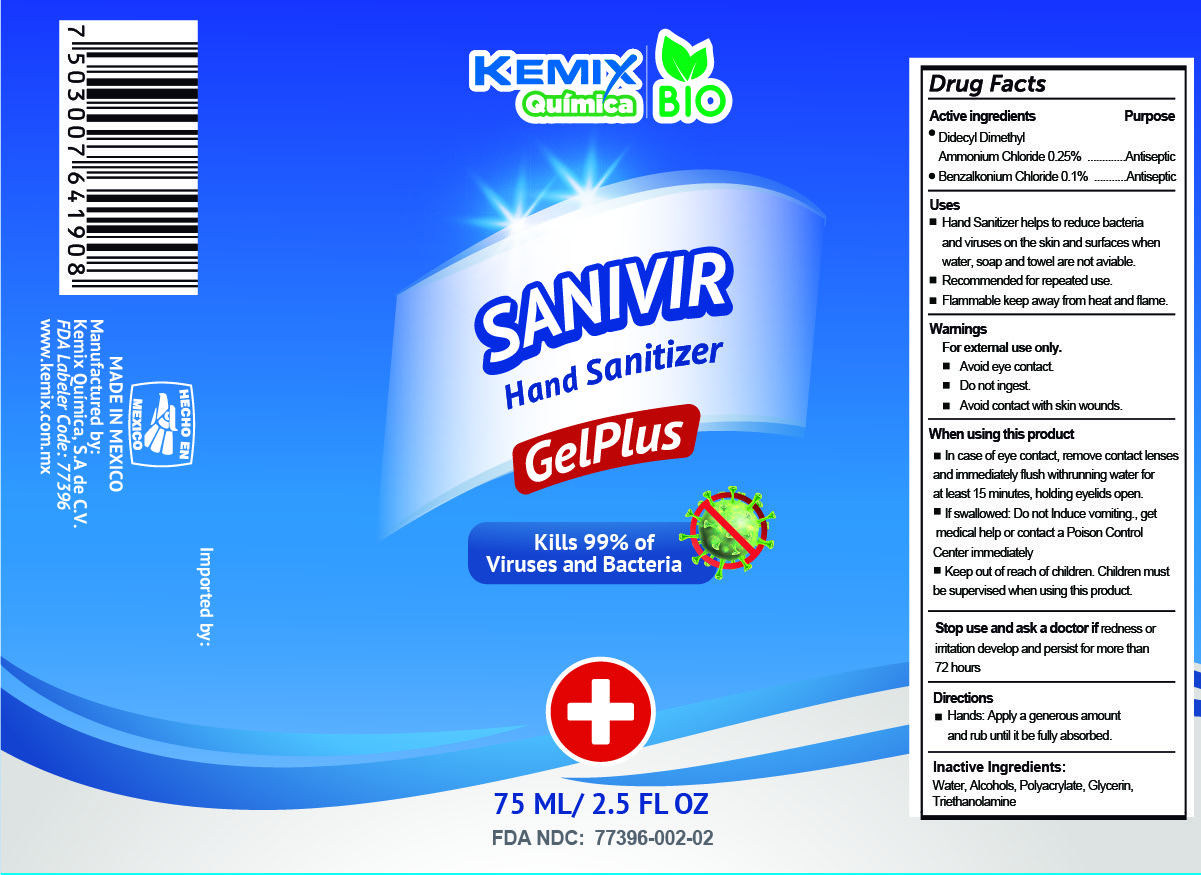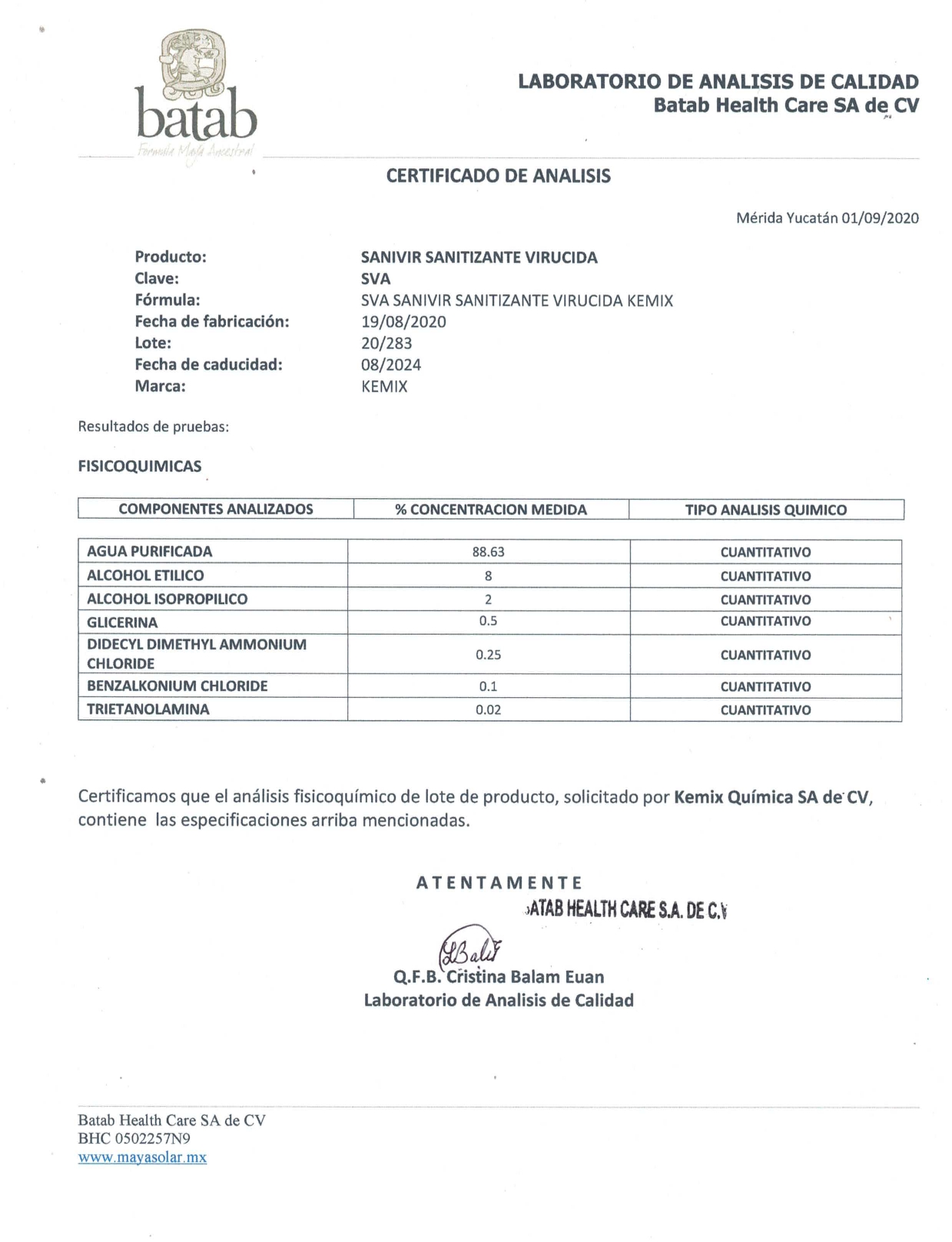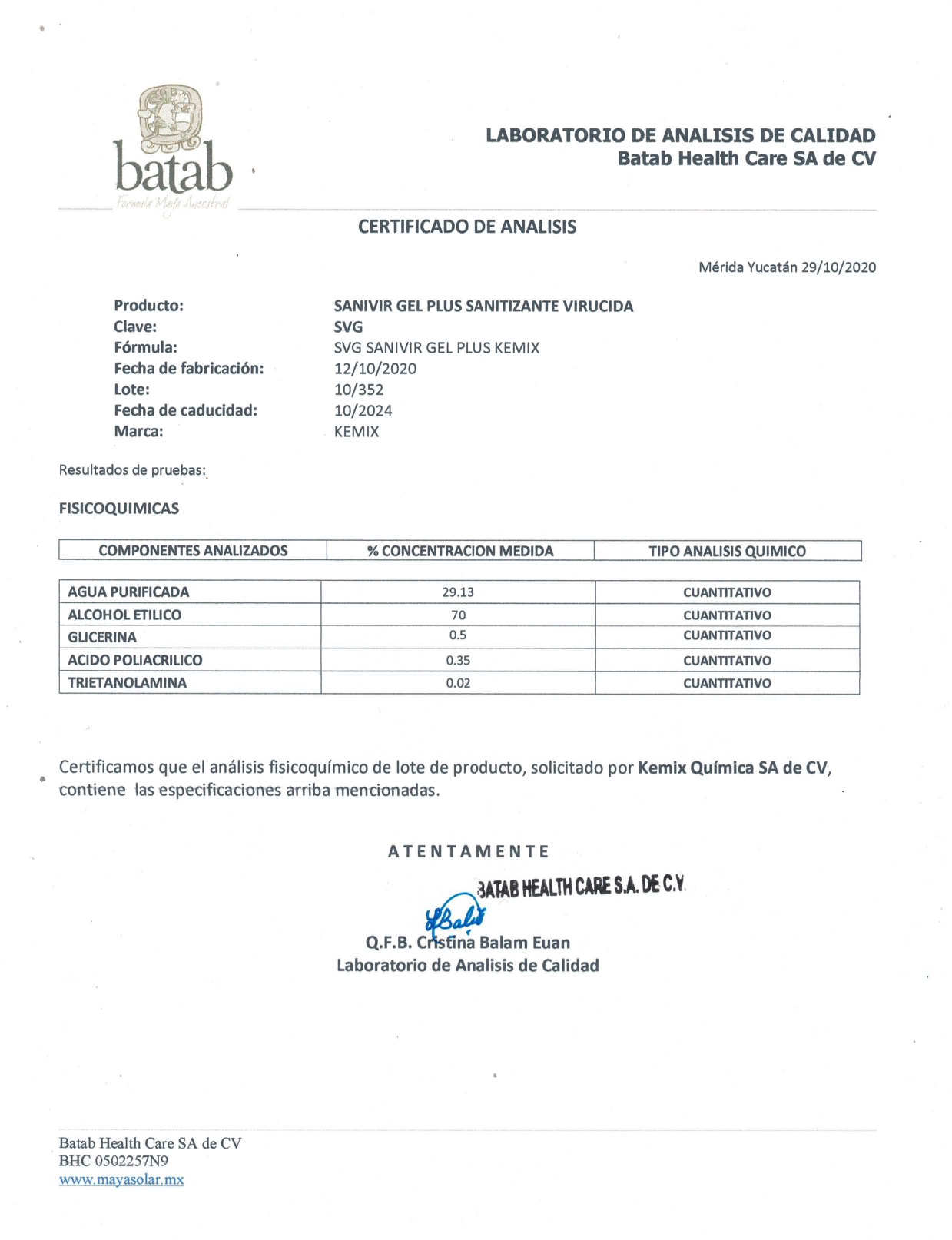 DRUG LABEL: SANIVIR Hands, Body, and Surfaces Sanitizer
NDC: 77396-001 | Form: LIQUID
Manufacturer: Kemix Quimica, S.A. de C.V.
Category: otc | Type: HUMAN OTC DRUG LABEL
Date: 20220120

ACTIVE INGREDIENTS: DIDECYLDIMONIUM CHLORIDE 2.5 mg/0.001 L; BENZALKONIUM CHLORIDE 1 mg/0.001 L
INACTIVE INGREDIENTS: TRIETHANOLAMINE TRIS(DIHYDROGEN PHOSPHATE); ALCOHOL; WATER; ISOPROPYL ALCOHOL; GLYCERIN

SANIVIR Sanitizer

SANIVIR Certificate of Analysis

SANIVIR Hands, Body and Surfaces - DATA SHEET

SANIVIR Gel Plus - DATA SHEET

DOSAGE AND ADMINISTRATION SECTION

WARNINGS

INACTIVE INGREDIENT SECTION

INACTIVE INGREDIENTS

INDICATIONS AND USAGE SECTION

KEEP OUT OF REACH OF CHILDREN SECTION

PURPOSE

OTC - PURPOSE SECTION

ACTIVE INGREDIENT

SANIVIR Hands, Body, and Surfaces Sanitizer 1,000 Lt (264 gallons)

77396-001-01

SANIVIR Hands, Body, and Surfaces Sanitizer 5Lt (1.32 gallons)

77396-001-02

SANIVIR Hands, Body, and Surfaces Sanitizer 75ml (2.4fl.oz)

NDC: 77396-01-003

SANIVIR Gel Plus Sanitizer 75ml (2.4fl.oz)

NDC: 77396-002-02

SANIVIR Gel Plus Sanitizer 5Lt (1.32gal)

NDC: 77396-002-01